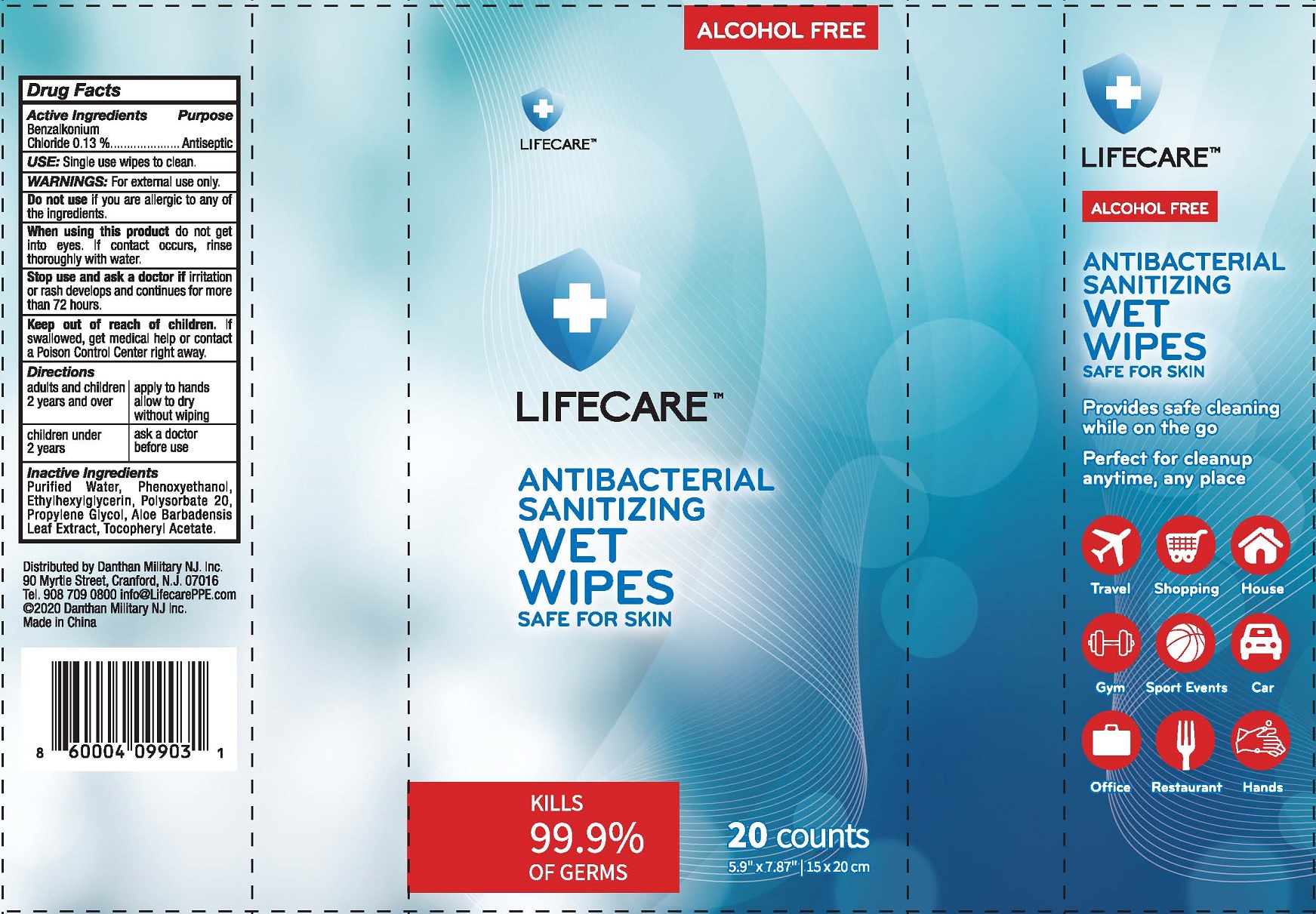 DRUG LABEL: LIFECARE Antibacterial Sanitizing Wet Wipes
NDC: 79680-006 | Form: SWAB
Manufacturer: Zhejiang Saiveroy Cleaning Products Co., LTD.
Category: otc | Type: HUMAN OTC DRUG LABEL
Date: 20201104

ACTIVE INGREDIENTS: BENZALKONIUM CHLORIDE 0.13 g/100 g
INACTIVE INGREDIENTS: WATER; PHENOXYETHANOL; ETHYLHEXYLGLYCERIN; POLYSORBATE 20; PROPYLENE GLYCOL; .ALPHA.-TOCOPHEROL ACETATE, D-

Wipes

Active Ingredient

Benzalkonium Chloride 0.13%

Purpose

Antiseptic

USE

Signle use wipes to clean.

Warning

- For external use only.
- Do not use if you are allergic to any of the ingredients.
- When using this product do not get into eyes. If contact occurs, rinse thoroughly with water.

- Stop use and ask a doctor, if irritaion or rash develops and continues for more than 72 hours.

KEEP OUT OF REACH OF CHILDREN

●If swallowed, get medical help or contact a Poison Contrl Center right away.

Directions

- adults and children 2 year and over - Apply to hands allow to dry without wiping.
- children under 2 years - ask a doctor before use.

Inactive ingredients

Purifed Water, Phenoxyethanol, Ethylhexylglycerin, Polysorbate 20, Propylene Glycol, Aloe Barbadensis Leaf Extract, Tocopheryl Acetate.